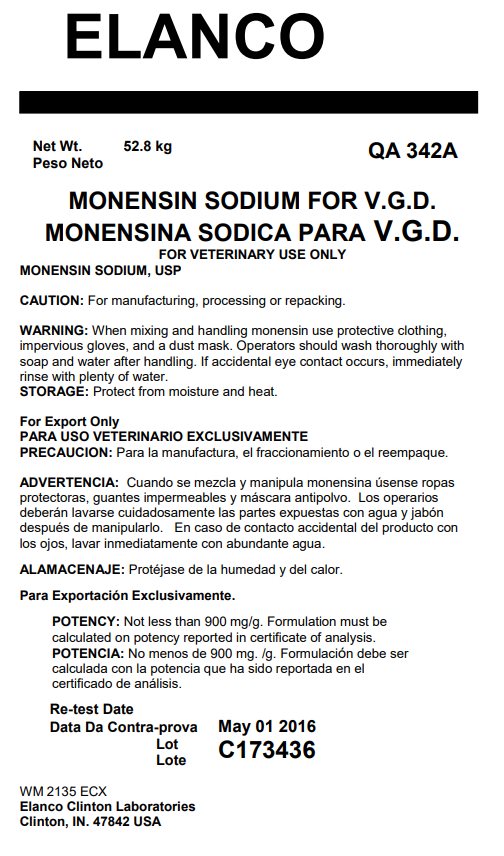 DRUG LABEL: Monensin Sodium
NDC: 58198-3420 | Form: POWDER
Manufacturer: Elanco US Inc.
Category: other | Type: BULK INGREDIENT - ANIMAL DRUG
Date: 20250708

ACTIVE INGREDIENTS: MONENSIN SODIUM 52.8 kg/52.8 kg

Monensin Sodium